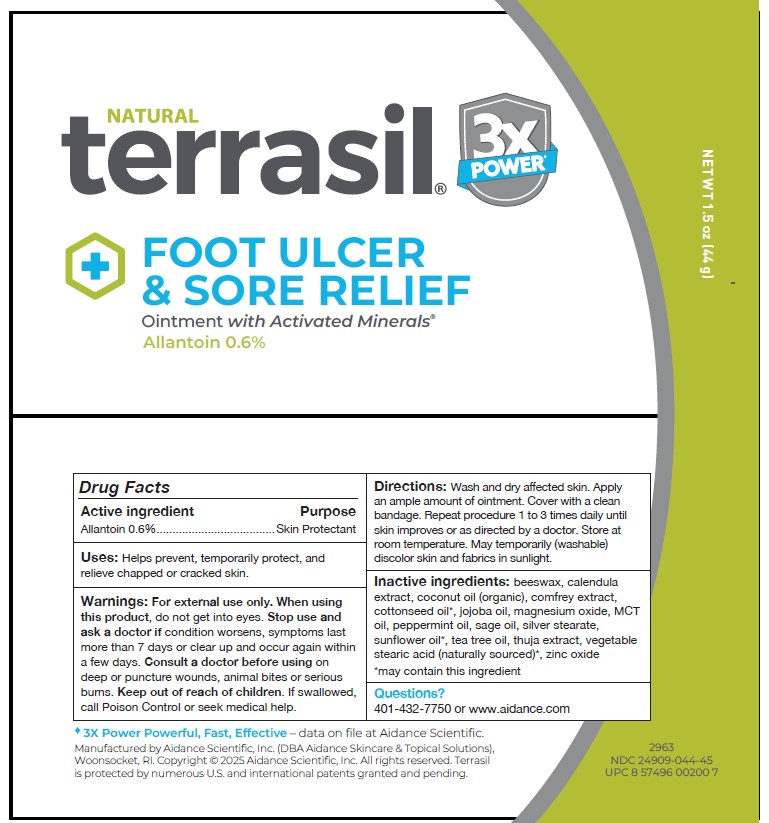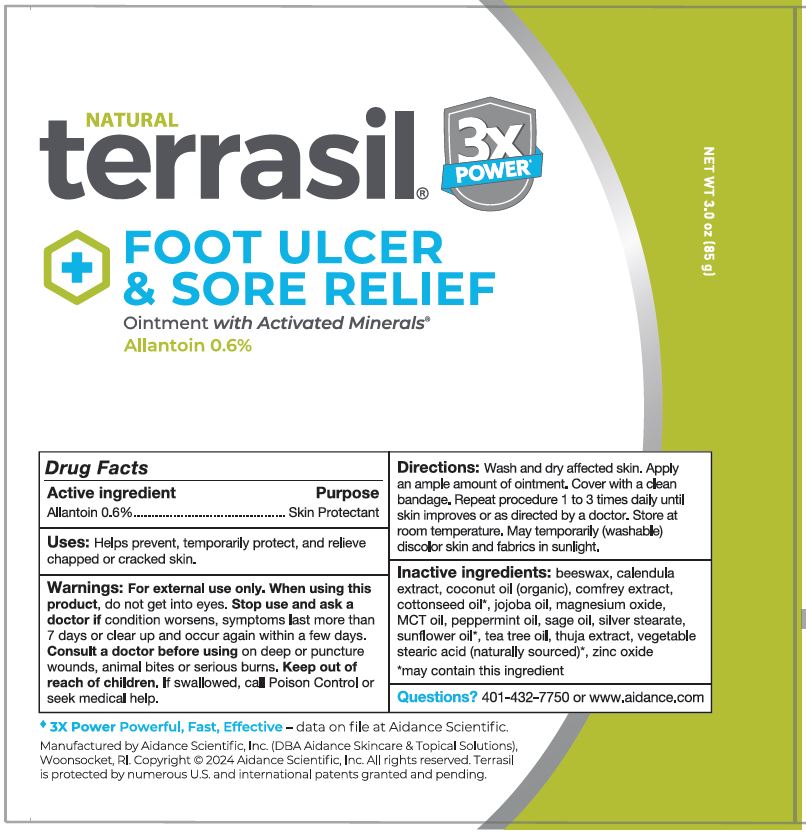 DRUG LABEL: terrasil Foot Ulcer and Sore Relief
NDC: 24909-044 | Form: OINTMENT
Manufacturer: Aidance Scientific, Inc., DBA Aidance Skincare & Topical Solutions
Category: otc | Type: HUMAN OTC DRUG LABEL
Date: 20251118

ACTIVE INGREDIENTS: ALLANTOIN 0.6 g/100 g
INACTIVE INGREDIENTS: COCONUT OIL; PALM OIL; SILVER STEARATE; THUJA OCCIDENTALIS LEAF; YELLOW WAX; CALENDULA OFFICINALIS FLOWER; COTTONSEED OIL; SUNFLOWER OIL; TEA TREE OIL; ZINC OXIDE; MAGNESIUM OXIDE; SAGE OIL; JOJOBA OIL; PEPPERMINT OIL; COMFREY ROOT

24909-044 terrasil Foot Ulcer & Sore Relief

Active ingredients

Allantoin 0.6%

Purpose

Skin Protectant

Uses

Helps prevent, temporarily protect, and relieve chapped or cracked skin.

Warnings

For external use only. When using this product,do not get into eyes. Stop use and ask a doctor ifcondition worsens, symptoms last more than 7 days or clear up and occur again within a few days. Consult a doctor before usingon deep or puncture wounds, animal bites or serious burns.

Keep out of reach of children.

OTHER SAFETY INFORMATION

If swallowed, call Poison Control or seek medical help.

Directions

Wash and dry affected skin. Apply an ample amount of ointment. Cover with a clean bandage. Repeat procedure 1 to 3 times daily until skin improves or as directed by a doctor. Store at room temperature. May temporarily (washable) discolor skin and fabrics in
sunlight.

Inactive ingredients

beeswax, calendula extract, coconut oil (organic), comfrey extract, cottonseed oil*, jojoba oil, magnesium oxide, MCT oil, peppermint oil, sage oil, silver stearate, sunflower oil*, tea tree oil, thuja extract, vegetable stearic acid (naturally sourced)*, zinc oxide

*May contain this ingredient